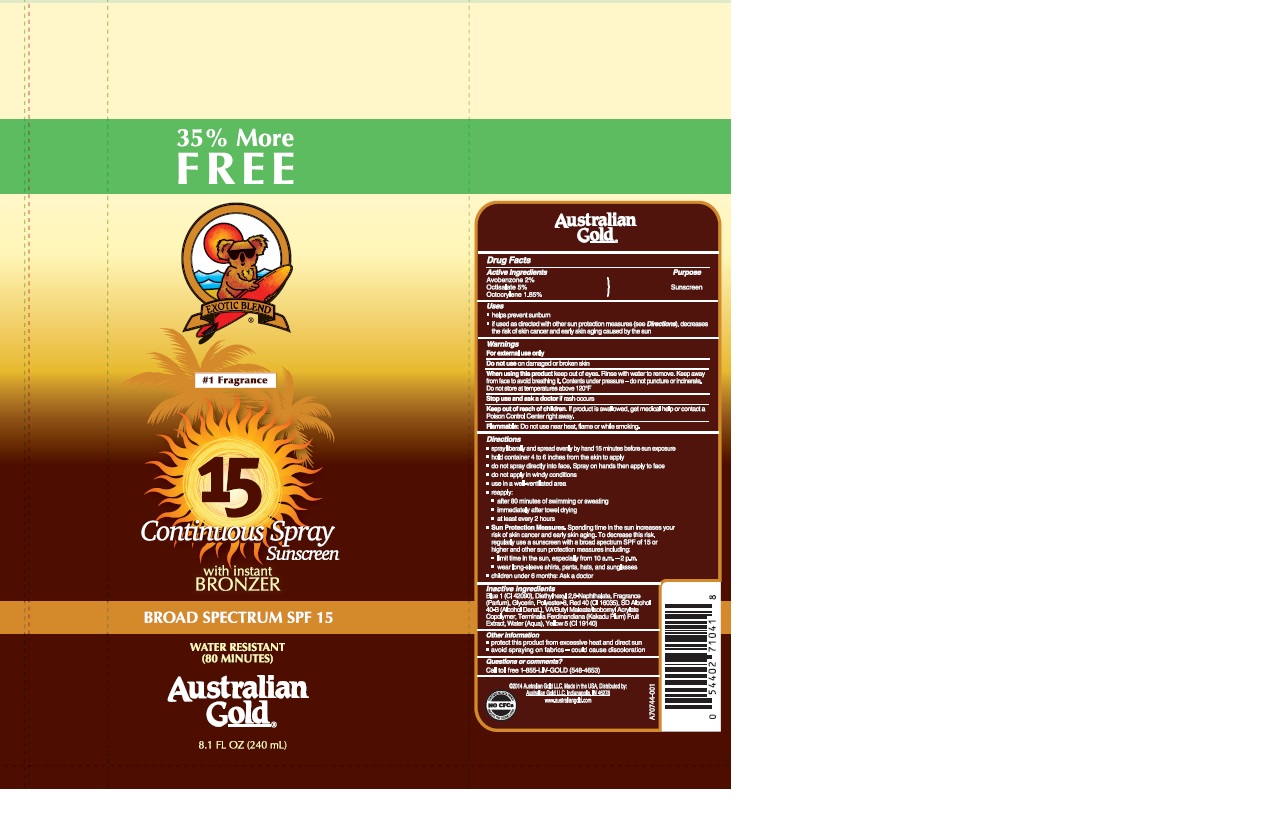 DRUG LABEL: Australian Gold
NDC: 13630-0101 | Form: SPRAY
Manufacturer: Prime Packaging Inc.
Category: otc | Type: HUMAN OTC DRUG LABEL
Date: 20200117

ACTIVE INGREDIENTS: AVOBENZONE 16.2 mg/1 mL; OCTISALATE 40.5 mg/1 mL; OCTOCRYLENE 15 mg/1 mL
INACTIVE INGREDIENTS: GLYCERIN; DIETHYLHEXYL 2,6-NAPHTHALATE; ALCOHOL; DIBUTYL MALEATE; WATER; POLYESTER-8 (1400 MW, CYANODIPHENYLPROPENOYL CAPPED); KAKADU PLUM

Australian Gold SPF 15 C/S Sunscreen with Bronzer

Active Ingredients

Avobenzone 2%

Octisalate 5%

Octocrylene 1.85%

Purpose

Sunscreen

Uses

- helps prevent sunburn
- if used as directed with other sun protection measures (see Directions), decreases the risk of skin cancer and early skin aging caused by the sun

Warnings

For external use only

Do not use on damaged or broken skin

When using this product keep out of eyes. Rinse with water to remove. Keep away from face to avoid breathing it. Contents under pressure - do not puncture or incinerate. Do not store at temperatures above 120°F

Stop use and ask a doctor if rash occurs

Keep out of reach of children. If product is swallowed, get medical help or contact a Poison Control Center right away.

Flammable: Do not use near heat, flame or while smoking.

Directions

- spray liberally and spread evenly by hand 15 minutes before sun exposure
- hold container 4 to 6 inches from the skin to apply
- do not spray directly into face. Spray on hands then apply to face
- do not apply in windy conditions
- use in a well-ventilated area
- reapply:
- after 80 minutes of swimming or sweating
- immediately after towel drying
- at least every 2 hours
- Sun Protection Measures. Spending time in the sun increases your risk of skin cancer and early skin aging. To decrease this risk, regularly use a sunscreen with a broad spectrum SPF of 15 or higher and other sun protection measures including:
- limit time in the sun, especially from 10 a. m. - 2 p. m.
- wear long-sleeve shirts, pants, hats, and sunglasses
- children under 6 months: Ask a doctor

INACTIVE INGREDIENT

Blue 1 (CI 42090), Diethylhexyl 2,6-Naphthalate, Fragrance (Parfum), Glycerin, Polyester-8, Red 40 (CI 16035), SD Alcohol 40-B (Alcohol Denat.), Terminalia Ferdinandiana (Kakadu Plum) Fruit Extract, VA/Butyl Maleate/Isobornyl Acrylate Copolymer, Water (Aqua), Yellow 5 (CI 19140)

Other Information

- protect this product from excessive heat and direct sun
- avoid spraying on fabrics - could cause discoloration

Question or comments?

Call toll free 1-855-LIV-GOLD (548-4653)